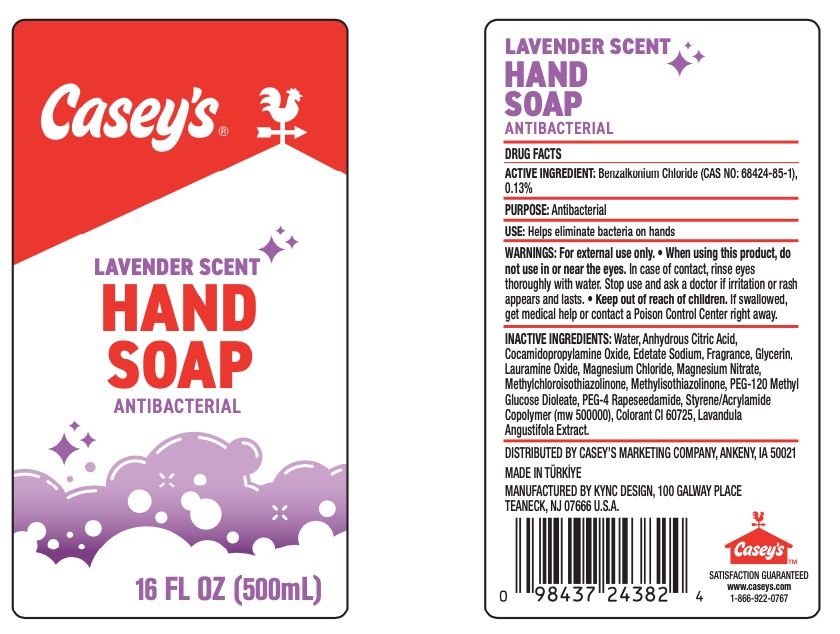 DRUG LABEL: CaseysLavender
NDC: 76557-051 | Form: LIQUID
Manufacturer: KYNC Design LLC
Category: otc | Type: HUMAN OTC DRUG LABEL
Date: 20260123

ACTIVE INGREDIENTS: BENZALKONIUM CHLORIDE 0.13 g/100 g
INACTIVE INGREDIENTS: LAVANDULA ANGUSTIFOLIA FLOWER; METHYLCHLOROISOTHIAZOLINONE; MAGNESIUM CHLORIDE; EDETATE SODIUM; COCAMIDOPROPYLAMINE OXIDE; WATER; MAGNESIUM NITRATE; PEG-4 RAPESEEDAMIDE; PEG-120 METHYL GLUCOSE DIOLEATE; ANHYDROUS CITRIC ACID; LAURAMINE OXIDE; METHYLISOTHIAZOLINONE; GLYCERIN; STYRENE/ACRYLAMIDE COPOLYMER (MW 500000)

Caseys Hand Soap

Active Ingredient(s)

Benzalkonium Chloride (CAS NO: 68424-85-1), 0.13% .

Purpose

Antimicrobial

Use

Helps eliminate bacteria on hands

WARNINGS

For external use only.

Do not use

If you are allergic to any of the ingredients.

Stop use and ask a doctor

if irritation or rash occurs.

Do not use in or near the eyes.

In case of contact, rinse eyes thoroughly with water. Stop use and ask a doctor if irritation or rash appears and lasts.

Keep out of reach of children.

If swallowed, get medical help or contact a poison control center immediately.

Directions

Wash hands and rinse

Inactive ingredients

Water, Anhydrous Citric Acid, Cocamidopropylamine Oxide, Edetate Sodium, Fragrance, Glycerin, Lauramine Oxide, Magnesium Chloride, Magnesium Nitrate, Methylchloroisothiazolinone, Methylisothiazolinone, PEG-120 Methyl Glucose Dioleate, PEG-4 Rapeseedamide, Styrene/acrylamide Copolymer (mw 500000), Colorant CI 60725, Lavandula Angustifola Extract.

PURPOSE

Antibacterial